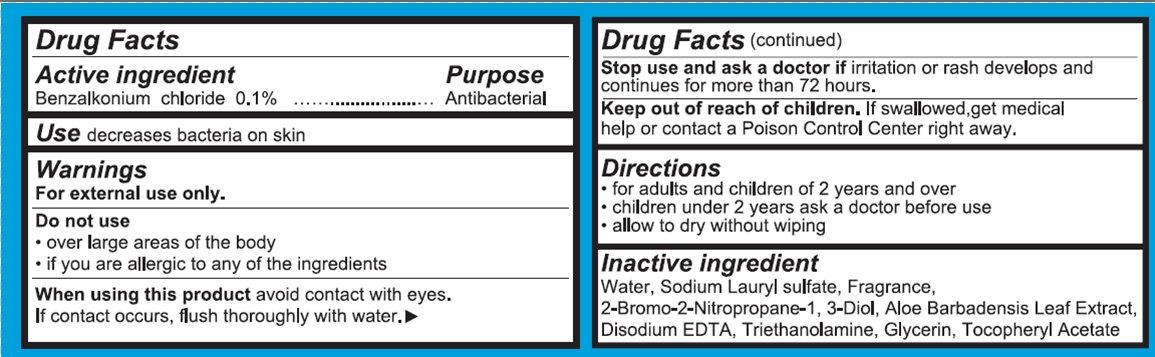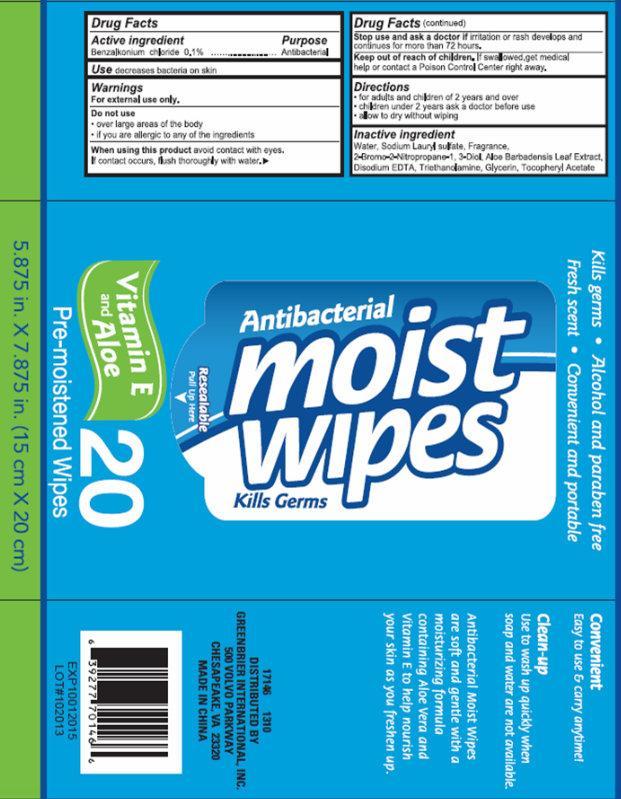 DRUG LABEL: Antibacterial Moist Wipe
                
NDC: 33992-2100 | Form: SWAB
Manufacturer: Greenbrier International, Inc.
Category: otc | Type: HUMAN OTC DRUG LABEL
Date: 20131010

ACTIVE INGREDIENTS: BENZALKONIUM CHLORIDE 1 mg/1 mL
INACTIVE INGREDIENTS: WATER; SODIUM LAURYL SULFATE; BRONOPOL; ALOE VERA LEAF; EDETATE DISODIUM; TROLAMINE; GLYCERIN; .ALPHA.-TOCOPHEROL ACETATE

Antibacterial Moist Wipes

Active Ingredient

Benzalkonium chloride 0.1%

Purpose

Antibacterial

Use

decreases bacteria on skin

Warnings

For external use only.

Do not use

- over large areas of the body
- if you are allergic to any of the ingredients

When using this product

avoid contact with eyes.

In contact occurs, flush thoroughly with water.

Stop use and ask a doctor if

irritation or rash develops and continues for more than 72 hours

Keep out of reach of children.

If swallowed, get medical help or contact a Poison Control Center right away.

Directions

- for adults and children of 2 years and over
- children under 2 years ask a doctor before use
- allow to dry without wiping

Inactive ingredient

Water, Sodium Lauryl sulfate, Fragrance, 2-Bromo-2-Nitropropane-1, 3-Diol, Aloe Barbadensis Leaf Extract, Disodium EDTA, Triethanolamine, Glycerin, Tocopheryl Acetate